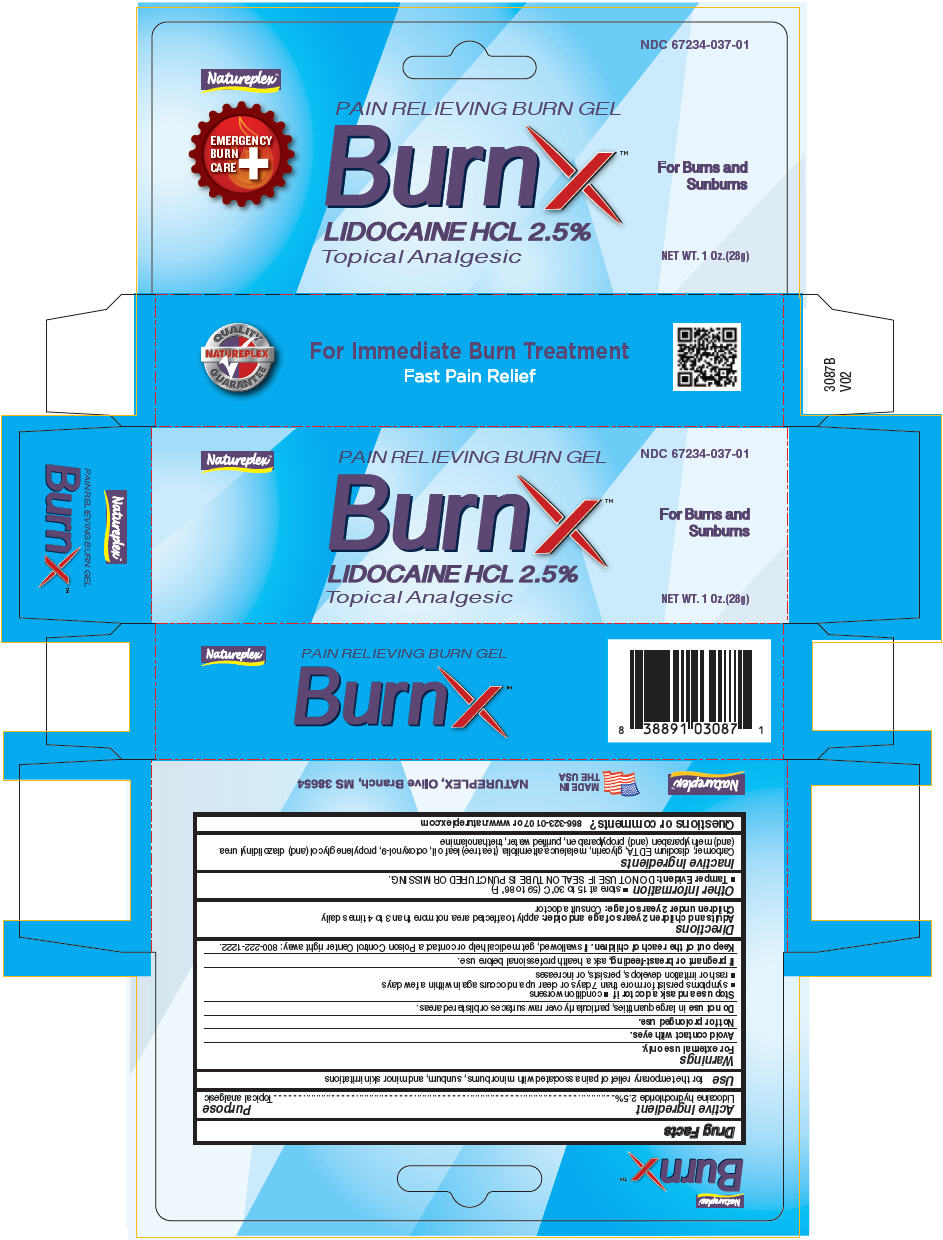 DRUG LABEL: BurnX 
NDC: 67234-037 | Form: GEL
Manufacturer: Natureplex, LLC
Category: otc | Type: HUMAN OTC DRUG LABEL
Date: 20171024

ACTIVE INGREDIENTS: LIDOCAINE HYDROCHLORIDE 0.025 g/1 g
INACTIVE INGREDIENTS: CARBOXYPOLYMETHYLENE; EDETATE DISODIUM ANHYDROUS; TEA TREE OIL; OCTOXYNOL-9; PROPYLENE GLYCOL; DIAZOLIDINYL UREA; METHYLPARABEN; PROPYLPARABEN; WATER; TROLAMINE; GLYCERIN

BurnX™
PAIN RELIEVING BURN GEL

Drug Facts

Active Ingredient

Lidocaine hydrochloride 2.5%

Purpose

Topical analgesic

Use

for the temporary relief of pain associated with minor burns, sunburn, and minor skin irritations

Warnings

For external use only.

Avoid contact with eyes.

Not for prolonged use.

Do not use in large quantities, particularly over raw surfaces or blistered areas.

Stop use and ask a doctor if

- condition worsens
- symptoms persist for more than 7 days or clear up and occurs again within a few days
- rash or irritation develops, persists, or increases

PREGNANCY OR BREAST FEEDING

If pregnant or breast-feeding, ask a health professional before use.

KEEP OUT OF REACH OF CHILDREN

Keep out of the reach of children. If swallowed, get medical help or contact a Poison Control Center right away: 800-222-1222.

Directions

Adults and children 2 years of age and older: apply to affected area not more than 3 to 4 times daily

Children under 2 years of age: Consult a doctor

Other Information

- store at 15 to 30° C (59 to 86° F)
- Tamper Evident: DO NOT USE IF SEAL ON TUBE IS PUNCTURED OR MISSING.

Inactive Ingredients

Carbomer, disodium EDTA, glycerin, melaleuca alternifolia (tea tree) leaf oil, octoxynol-9, propylene glycol (and) diazolidinyl urea (and) methylparaben (and) propylparaben, purified water, triethanolamine

Questions or comments?

866-323-0107 or www.natureplex.com

PRINCIPAL DISPLAY PANEL - 28 g Tube Carton

Natureplex™

PAIN RELIEVING BURN GEL
NDC 67234-037-01

BurnX™
LIDOCAINE HCL 2.5%
Topical Analgesic

For Burns and
Sunburns

NET WT. 1 Oz.(28g)